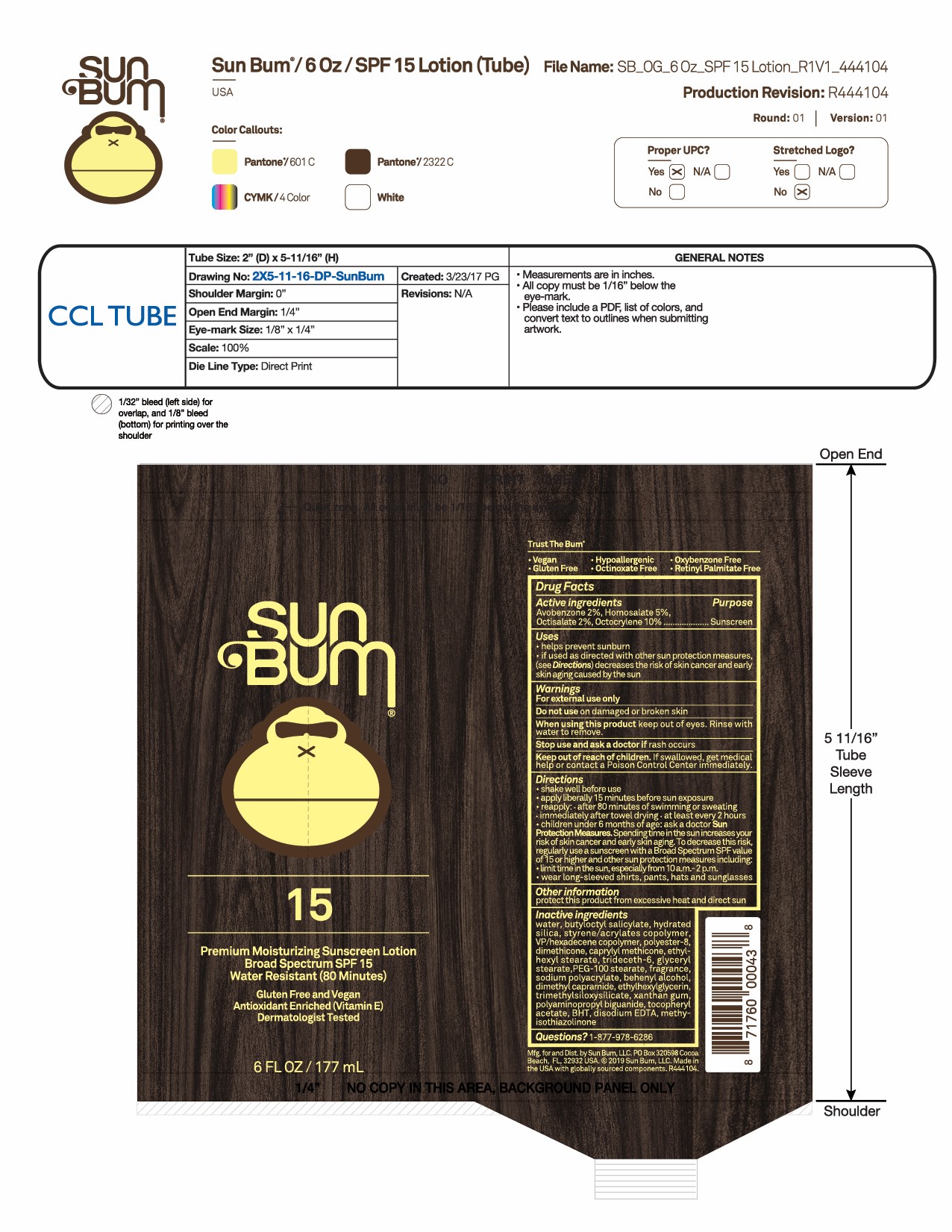 DRUG LABEL: Premium Moisturizing Sunscreen Broad Spectrum SPF 15
NDC: 44717-072 | Form: LOTION
Manufacturer: Wasatch Product Development, LLC
Category: otc | Type: HUMAN OTC DRUG LABEL
Date: 20251009

ACTIVE INGREDIENTS: OCTOCRYLENE 10 g/100 mL; AVOBENZONE 2 g/100 mL; HOMOSALATE 5 g/100 mL; OCTISALATE 2 g/100 mL
INACTIVE INGREDIENTS: POLYESTER-8 (1400 MW, CYANODIPHENYLPROPENOYL CAPPED); EDETATE DISODIUM ANHYDROUS; BUTYLOCTYL SALICYLATE; DIMETHYL CAPRAMIDE; XANTHAN GUM; .ALPHA.-TOCOPHEROL ACETATE; TRIMETHYLSILOXYSILICATE (M/Q 0.6-0.8); BUTYLATED HYDROXYTOLUENE; METHYLISOTHIAZOLINONE; VINYLPYRROLIDONE/HEXADECENE COPOLYMER; DIMETHICONE 100; CAPRYLYL TRISILOXANE; TRIDECETH-6; GLYCERYL MONOSTEARATE; HYDRATED SILICA; PEG-100 STEARATE; SODIUM POLYACRYLATE (2500000 MW); DOCOSANOL; ETHYLHEXYLGLYCERIN; POLYAMINOPROPYL BIGUANIDE; WATER; ETHYLHEXYL STEARATE

Sun Bum SPF 15 Premium Moisturizing Sunscreen Lotion

Active ingredients

Avobenzone 2%, Homosalate 5%,

Octisalate 2%, Octocrylene 10% Purpose: Sunscreen

Uses

- helps prevent sunburn
- If used as directed with other sun protection measures (see Directions), decreases the risk of skin cancer and early skin aging caused by the sun.

Keep out of reach of children. If swallowed, get medical help or contact a Poison Control Center immediately.

Stop use and ask a doctor if rash occurs

WARNINGS

For external use only
Do not use on damaged or broken skin
When using this product keep out of eyes. Rinse with water to remove

Directions

- shake well before use
- apply liberally 15 minutes before sun exposure
- reapply:
- after 80 minutes of swimming or sweating
- immediately after towel drying
- at least every 2 hours.
- children under 6 months of age: ask a doctor.
- Sun Protection Measures Spending time in the sun increases your risk of

skin cancer and early skin aging. To decrease this risk, regularly use a
sunscreen with a Broad-Spectrum SPF value of 15 or higher and other sun
protection measures including:

• limit your time in the sun, especially from 10a.m. – 2 p.m.
• wear long-sleeved shirts, pants, hats, and sunglasses

OTHER SAFETY INFORMATION

Protect this product from excessive heat and direct sun

Inactive ingredients

water, butyloctyl salicylate, hydrated silica, styrene/acrylates copolymer, VP/hexadecene copolymer, polyester-8, dimethicone, caprylyl methicone, ethylhexyl stearate, trideceth-6, glyceryl stearate, PEG-100 stearate, fragrance, sodium polyacrylate, behenyl alcohol, dimethyl capramide, ethylhexylglycerin, trimethylsiloxysilicate, xanthan gum, polyaminopropyl biguanide, tocopheryl acetate, BHT, disodium EDTA, methylisothiazolinone

PACKAGE LABEL

Sun Bum

15

Premium Moisturizing Sunscreen Lotion Broad Spectrum SPF 15

Water Resistant (80 Minutes)

Gluten Free and Vegan

Antioxidant Enriched (Vitamin E)

Dermatologist Tested

6 FL OZ / 177 mL